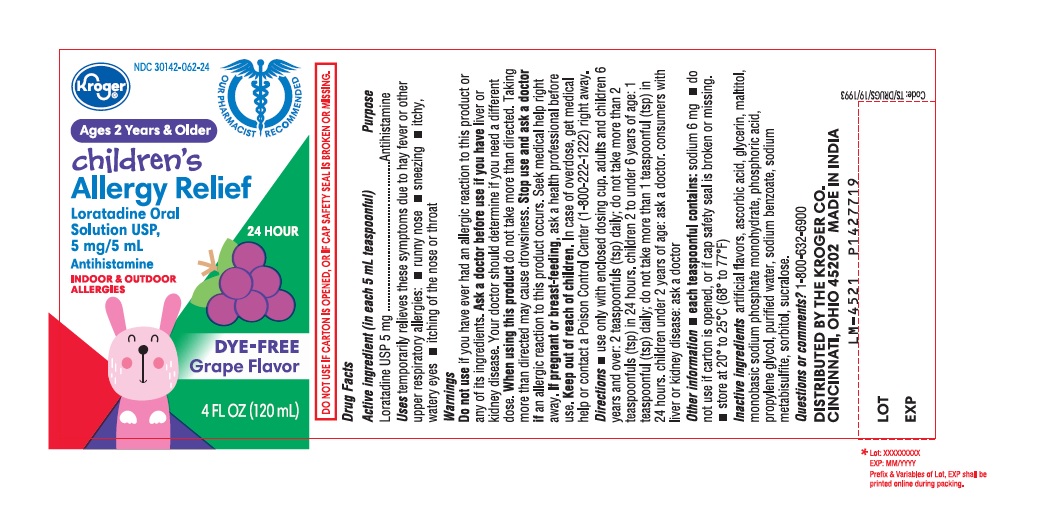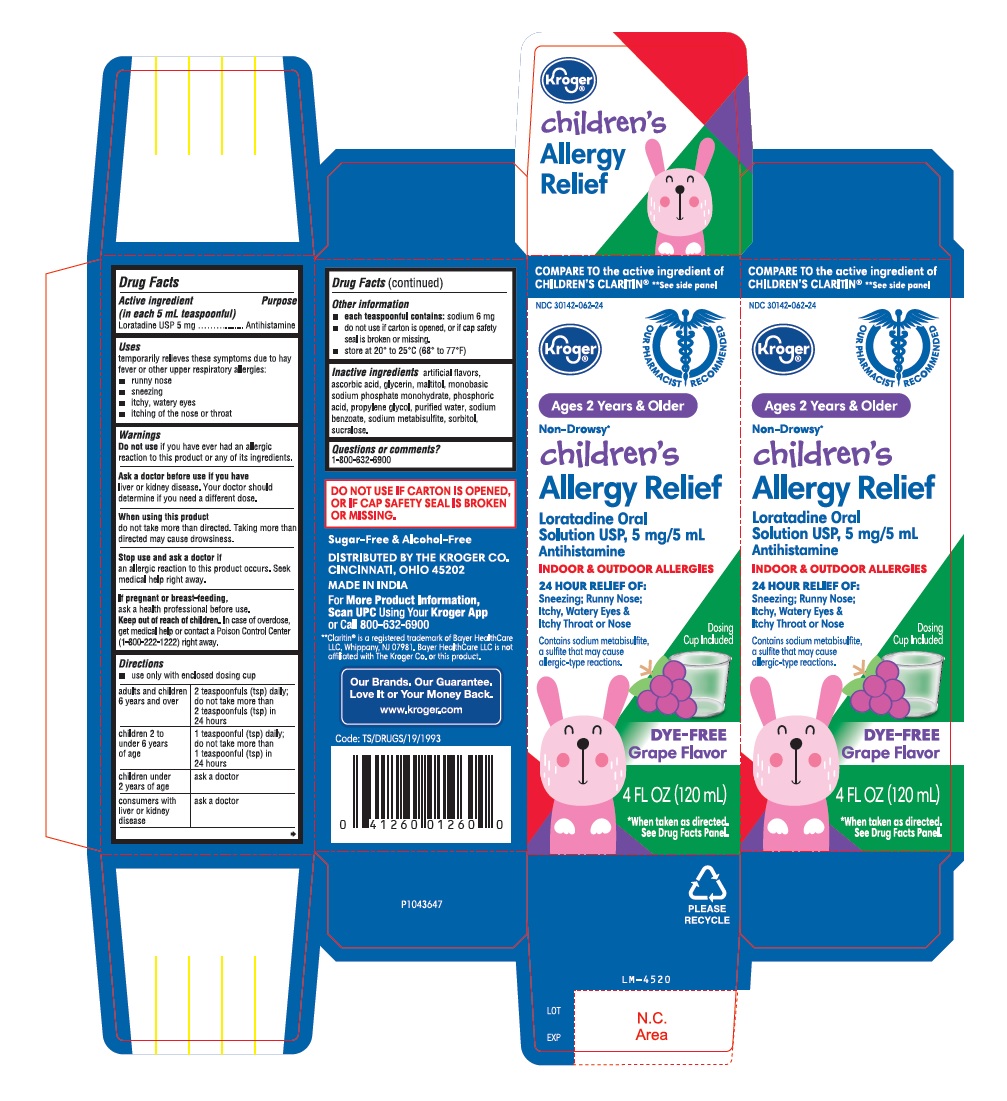 DRUG LABEL: Loratadine
NDC: 30142-062 | Form: SOLUTION
Manufacturer: KROGER COMPANY
Category: otc | Type: Human OTC Drug Label
Date: 20210419

ACTIVE INGREDIENTS: LORATADINE 5 mg/5 mL
INACTIVE INGREDIENTS: GRAPE; ASCORBIC ACID; GLYCERIN; MALTITOL; SODIUM PHOSPHATE, MONOBASIC, MONOHYDRATE; PHOSPHORIC ACID; PROPYLENE GLYCOL; WATER; SODIUM BENZOATE; SODIUM METABISULFITE; SORBITOL; SUCRALOSE

Loratadine Oral Solution USP 5 mg/5 mL

Drug Facts

Active ingredient (in each 5 mL teaspoonful)
Loratadine USP 5 mg

Purpose

Antihistamine

Uses

temporarily relieves these symptoms due to hay fever or other upper respiratory allergies:

- runny nose
- sneezing
- itchy, watery eyes
- itching of the nose or throat

Warnings

Do not use if you have ever had an allergic reaction to this product or any of its ingredients.

Ask a doctor before use if you have

liver or kidney disease. Your doctor should determine if you need a different dose.

When using this product

do not take more than directed. Taking more than directed may cause drowsiness.

Stop use and ask a doctor if

an allergic reaction to this product occurs. Seek medical help right away.

If pregnant or breast-feeding,

ask a health professional before use.

Keep out of reach of children.

In case of overdose, get medical help or contact a Poison Control Center (1-800-222-1222) right away.

Directions

- use only with enclosed dosing cup

adults and children 6 years and over | 2 teaspoonfuls (tsp) daily; do not take more than 2 teaspoonfuls (tsp) in 24 hours
children 2 to under 6 years of age | 1 teaspoonful (tsp) daily; do not take more than 1 teaspoonful (tsp) in 24 hours
children under 2 years of age | ask a doctor
consumers with liver or kidney disease | ask a doctor

Other information

- each teaspoonful contains: sodium 6 mg
- do not use if carton is opened, or if cap safety seal is broken or missing.
- store at 20° to 25°C (68° to 77°F)

Inactive ingredients

artificial flavors, ascorbic acid, glycerin, maltitol, monobasic sodium phosphate monohydrate, phosphoric acid, propylene glycol, purified water, sodium benzoate, sodium metabisulfite, sorbitol, sucralose.

Questions or comments?

1-800-632-6900
DISTRIBUTRD BY THE KROGER CO.
CINCINNATI, OHIO 45202
MADE IN INDIA
Code:TS/DRUGS/19/1993

PACKAGE LABEL-PRINCIPAL DISPLAY PANEL - 5 mg/5 mL (120 mL Bottle)

NDC 30142-062-24
Kroger®
Ages 2 Years & Older

children's
Allergy Relief

Loratadine Oral
Solution USP,
5 mg/5 mL
Antihistamine
INDOOR & OUTDOOR
ALLERGIES

24 HOUR
DYE-FREE
Grape Flavor
4 FL OZ (120 mL)

PACKAGE LABEL-PRINCIPAL DISPLAY PANEL - 5 mg/5 mL Carton (120 mL)

COMPARE TO the active ingredient of
CHILDRENS'S CLARITIN® **See side panel
NDC 30142-062-24

Kroger®
Ages 2 Years & Older
Non-Drowsy*
children's
Allergy Relief
Loratadine Oral
Solution USP, 5 mg/5 mL
Antihistamine
INDOOR & OUTDOOR ALLERGIES
24 HOUR RELIEF OF:

Sneezing; Runny Nose;
Itchy,watery Eyes &
Itchy Throat or Nose
Contains sodium metabisulfite,
a sulfite that may cause
allergic-type reactions.
Dosing
Cup Included

DYE-FREE
Grape Flavor
4 FL OZ (120 mL)

* When taken as directed.

See Drug Facts Panel.